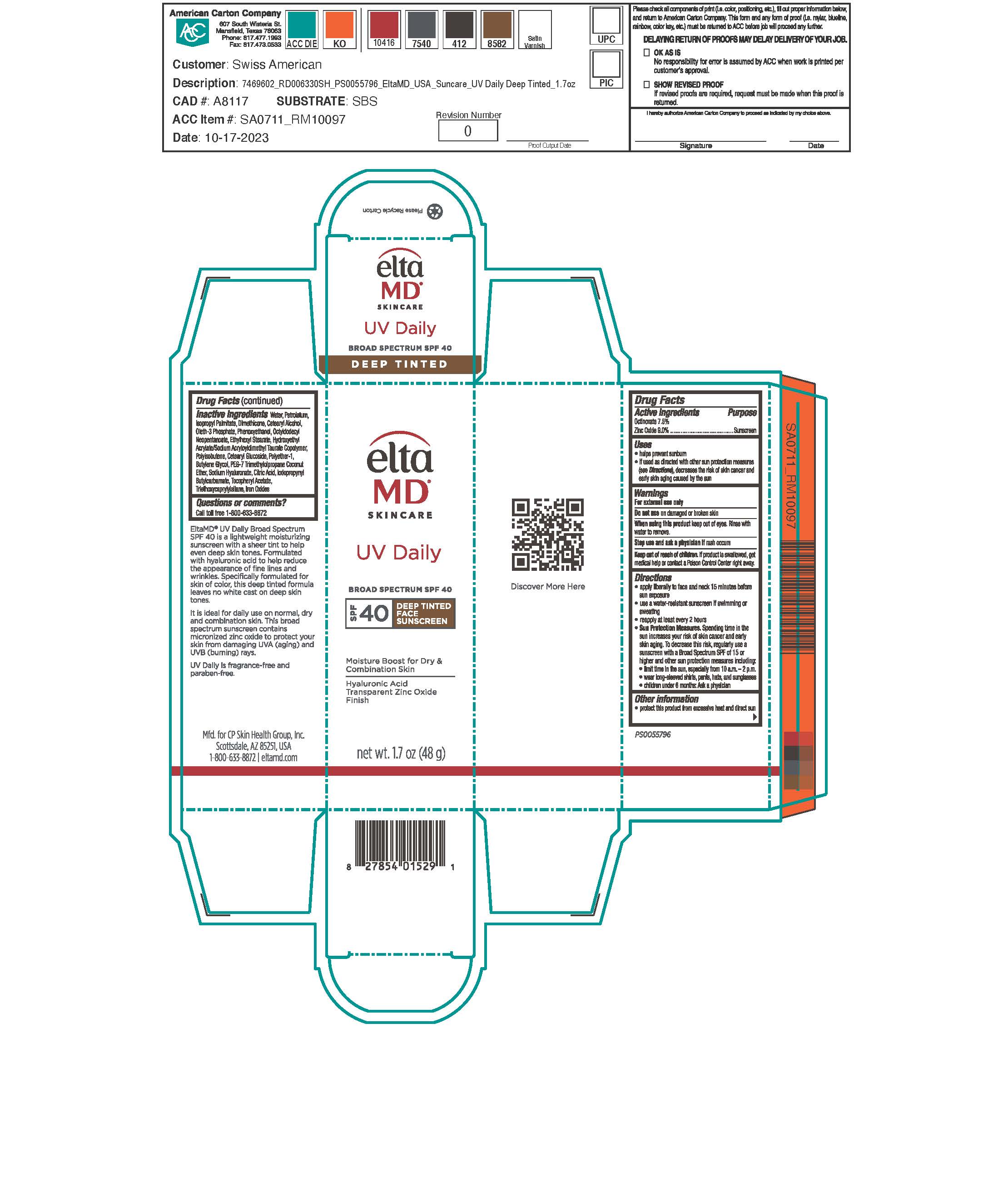 DRUG LABEL: UV Daily Deep Tint
NDC: 72043-2920 | Form: LOTION
Manufacturer: CP Skin Health Group, Inc.
Category: otc | Type: HUMAN OTC DRUG LABEL
Date: 20240509

ACTIVE INGREDIENTS: OCTINOXATE 750 g/1000 g; ZINC OXIDE 900 g/1000 g
INACTIVE INGREDIENTS: WATER; PHENOXYETHANOL; DIMETHICONE; PETROLATUM; ISOPROPYL PALMITATE; BUTYLATED HYDROXYTOLUENE; OLETH-3 PHOSPHATE; PHOSPHORIC ACID; ETHYLHEXYL STEARATE; OCTYLDODECYL NEOPENTANOATE; FERRIC OXIDE YELLOW; FERRIC OXIDE RED; FERROSOFERRIC OXIDE; TRIETHOXYCAPRYLYLSILANE; CETEARYL GLUCOSIDE; CETOSTEARYL ALCOHOL; CITRIC ACID MONOHYDRATE; HYDROXYETHYL ACRYLATE/SODIUM ACRYLOYLDIMETHYL TAURATE COPOLYMER (100000 MPA.S AT 1.5%); POLYISOBUTYLENE (1000 MW); .ALPHA.-TOCOPHEROL ACETATE; HYALURONIC ACID; PEG-7 TRIMETHYLOLPROPANE COCONUT ETHER; BUTYLENE GLYCOL; IODOPROPYNYL BUTYLCARBAMATE

EltaMD UV Daily Deep Tint

Warnings

For external use only. Do not use on damaged or broken skin. When using this product keep out of eyes. Rinse with water to remove. Stop use and ask a physician if rash occurs. If product is swallowed get medical help or contact a Poison Control Center right away.

Keep out of reach of children

Uses

Helps prevent sunburn. If used as directed with other sun protection measure (See Directions), decreases the risk of skin cancer and early skin aging caused by the sun.

Uses

Helps prevent sunburn. If used as directed with other sun protection measure (See Directions), decreases the risk of skin cancer and early skin aging caused by the sun.

Directions

Apply liberally 15 minutes before sun exposure. Use a water-resistant sunscreen if swimming or sweating. Reapply at least every 2 hours. Sun Protection Measures: Spending time in the sun increases your risk of skin cancer and early skin aging. To decrease this risk, regularly use a sunscreen with a broad-spectrum SPF of 15 or higher and other sun protection measures including: limit time in the sun, especially from 10 am to 2 pm. Wear long-sleeve shirts, pants, hats, and sunglasses. Children under 6 months: ask a physician.

Active Ingredients

Octinoxate 7.5%

Zinc Oxide 9.0%

Inactive Ingredients

water, petrolatum, isopropyl palmitate, dimethicone, cetearyl alcohol, oleth-3 phosphate, phenoxyethanol, octyldodecyl neopentanoate, ethylhexyl stearate, hydroxyethyl acrylate/sodium acryloyldimethyl taurate copolymer, polyisobutene, cetearyl glucoside, polyether-1, butylene glycol, PEG-7 trimethylolpropane cocnut ether, sodium hyaluronate, citric acid, iodopropynyl butylcarbamate, tocopheryl acetate, triethoxycaprylylsilane, iorn oxides

Questions

Call toll free 1-800-633-8872